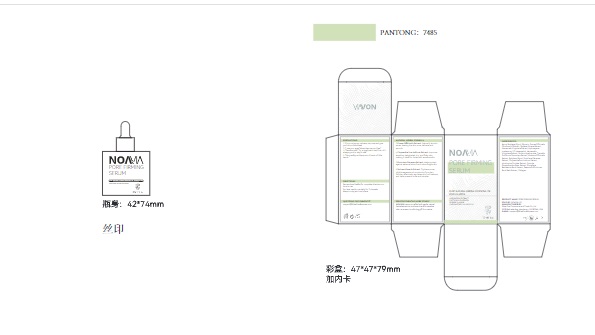 DRUG LABEL: NOAVIA PORE FIRMING SERUM
NDC: 85212-0013 | Form: LIQUID
Manufacturer: Beijing JUNGE Technology Co., Ltd.
Category: otc | Type: HUMAN OTC DRUG LABEL
Date: 20250226

ACTIVE INGREDIENTS: FIELD MUSHROOM 3 g/100 mL; HAMAMELIS VIRGINIANA (WITCH HAZEL) LEAF WATER 2 g/100 mL
INACTIVE INGREDIENTS: VERBENA OFFICINALIS 1 mL/100 mL; PAEONIA SUFFRUTICOSA ROOT 0.1 mL/100 mL; HOUTTUYNIA CORDATA WHOLE 0.5 mL/100 mL; CHRYSANTHEMUM INDICUM WHOLE 3 mL/100 mL; SODIUM HYALURONATE 1 mL/100 mL; AQUA 73.2 mL/100 mL; HYDROXYACETOPHENONE 2 mL/100 mL; GLYCERIN 5 mL/100 mL; OPUNTIA STREPTACANTHA STEM 0.1 mL/100 mL; SCUTELLARIA BAICALENSIS ROOT 0.1 mL/100 mL; 1,2-HEXANEDIOL 2 mL/100 mL; CHRYSANTHELLUM INDICUM WHOLE 0.5 mL/100 mL; BUTYLENE GLYCOL 5 mL/100 mL; TREMELLA FUCIFORMIS WHOLE 1 mL/100 mL; PORTULACA OLERACEA WHOLE 0.5 mL/100 mL

PRECAUTIONS

If you notice any redness, stop use and give your skin a little break.

"Love your eyes? Keep them serum-free!"
"Sensitive skin? Try a small patch test first—it’s
always good to play it safe."
"Store safely and keep out of reach of little hands."

INDICATIONS AND USAGE

BOTANICAL PURITY FOR A YOUTHFUL COMPLEXION

SOOTHES, PROTECTS, AND BALANCES SENSITIVE SKIN

It relieves dry, flaky skin and protects against irritation and harmful microbes, restoring balance to your skin.

QUESTIONS

support@WiseOneBusiness.com

ACTIVE INGREDIENT

FOMES OFFICINALIS (MUSHROOM) EXTRACT
HAMAMELIS VIRGINIANA (WITCH HAZEL) EXTRACT
SODIUM HYALURONATE

INACTIVE INGREDIENT

AQUA
BUTYLENE GLYCOL
GLYCERIN
SPIRAEA ULMARIA EXTRACT
HYDROXYACETOPHENONE
1,2-HEXANEDIOL
TREMELLA FUCIFORMIS SPOROCARP EXTRACT
VERBENA OFFICINALIS EXTRACT
BUTYLENE GLYCOL
PORTULACA OLERACEA EXTRACT
CHRYSANTHELLUM INDICUM EXTRACT
HOUTTUYNIA CORDATA EXTRACT
OPUNTIA STREPTACANTHA STEM EXTRACT
SCUTELLARIA BAICALENSIS ROOT EXTRACT
PAEONIA SUFFRUTICOSA ROOT EXTRACT

WARNINGS

For external use only. Keep out of reach of children.Avoid contact with eyes.

Keep out of reach of children. If swallowed, get medical help or contact a Poison Control Center right away

DOSAGE AND ADMINISTRATION

30ml/1fl.oz

PURPOSE

EFFECTIVE BLACKHEAD AND PORE CARE

BOTANICAL PURITY FOR A YOUTHFUL COMPLEXION

INTENSE HYDRATION AND SKIN RESILIENCE